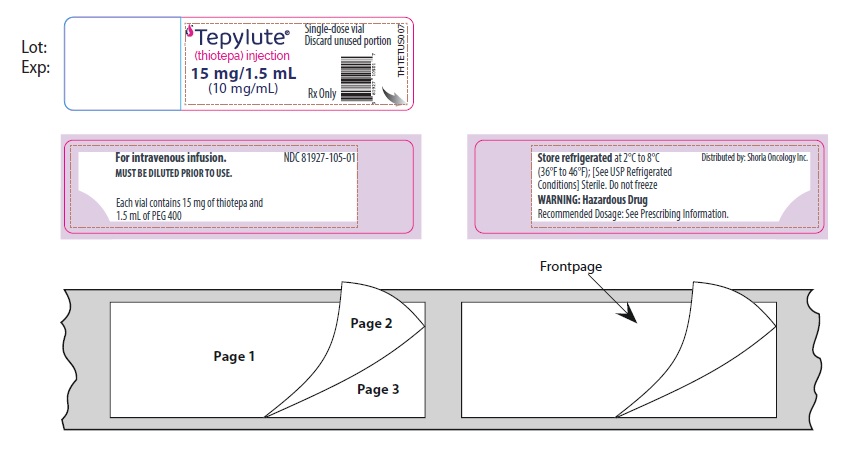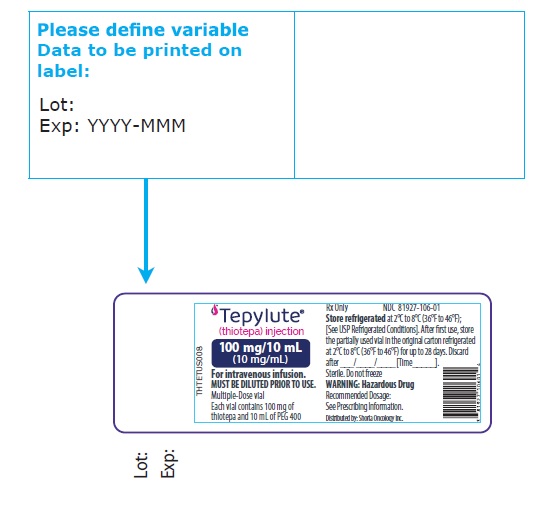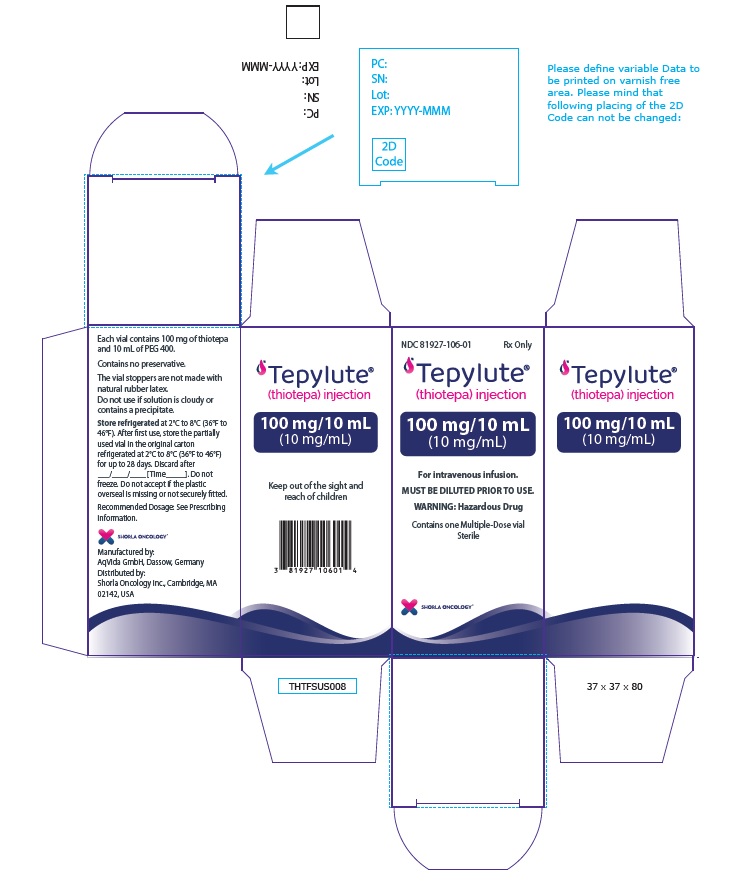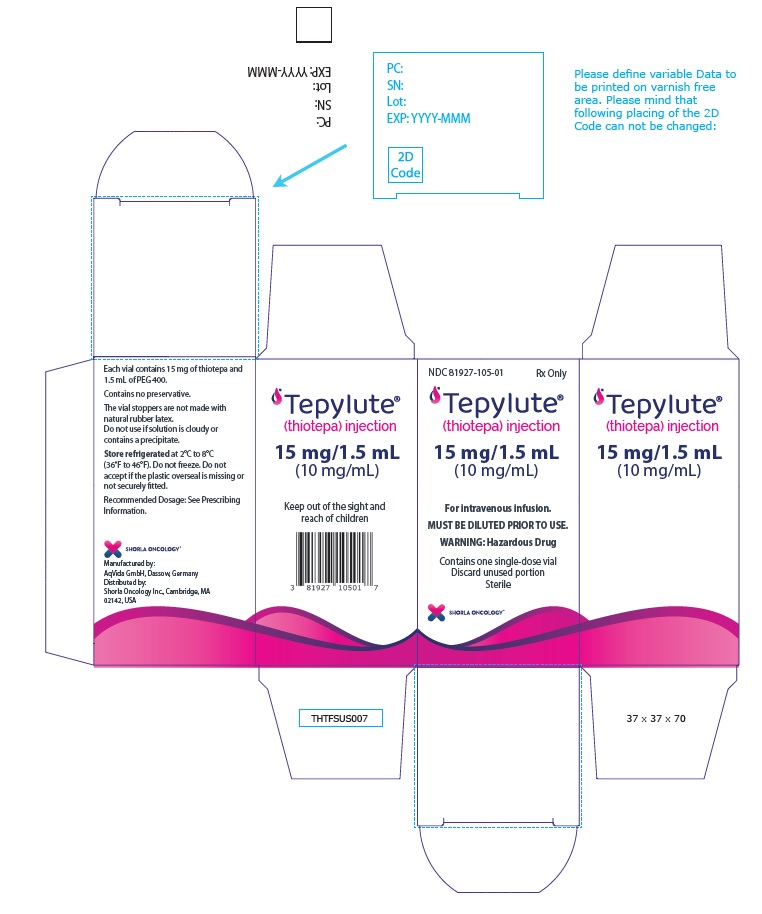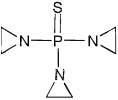 DRUG LABEL: TEPYLUTE
NDC: 81927-105 | Form: INJECTION
Manufacturer: Shorla Oncology Inc.
Category: prescription | Type: HUMAN PRESCRIPTION DRUG LABEL
Date: 20250701

ACTIVE INGREDIENTS: THIOTEPA 10 mg/1 mL
INACTIVE INGREDIENTS: POLYETHYLENE GLYCOL 400

HIGHLIGHTS OF PRESCRIBING INFORMATION

These highlights do not include all the information needed to use TEPYLUTE® safely and effectively. See full prescribing information for TEPYLUTE®.
TEPYLUTE® (thiotepa) injection, for intravenous use
Initial U.S. Approval: 1959

RECENT MAJOR CHANGES

Dosage and Administration (2.2) 7/2025

WARNING: SEVERE MYELOSUPPRESSION and CARCINOGENICITY

See full prescribing information for complete boxed warning

- May cause severe marrow suppression or ablation with resulting infection or bleeding. Monitor hematologic laboratory parameters (5.1).
- Potentially carcinogenic in humans (5.7).

1 INDICATIONS AND USAGE

TEPYLUTE is an alkylating drug indicated for treatment of adenocarcinoma of the breast or ovary. (1.1)

2 DOSAGE AND ADMINISTRATION

The recommended dose of TEPYLUTE for treatment of adenocarcinoma of the breast or ovary is 0.3 mg/kg to 0.4 mg/kg intravenously. (2.1)

See full prescribing information for preparation instructions. (2.2)

3 DOSAGE FORMS AND STRENGTHS

- Injection: 15 mg/1.5 mL (10 mg/mL) of thiotepa solution in single-dose vial. (3)
- Injection: 100 mg/10 mL (10 mg/mL) of thiotepa solution in multiple-dose vial (3).

4 CONTRAINDICATIONS

- Hypersensitivity to the active substance. (4)
- Concomitant use with live or attenuated vaccines. (4)

5 WARNINGS AND PRECAUTIONS

- Cutaneous Toxicity: Cleanse skin at least twice daily through 48 hours after the last dose of TEPYLUTE. (5.3)
- Polyethylene Glycol 400 Toxicity: Take into consideration the PEG 400 load from concomitant medications. (5.8)
- Embryo-Fetal Toxicity: Can cause fetal harm. Advise females of reproductive potential of the potential risk to a fetus and to use effective contraception. (5.9)

6 ADVERSE REACTIONS

The most common adverse reactions (incidence greater than 10%) are neutropenia, anemia, thrombocytopenia, elevated alanine aminotransferase, elevated aspartate aminotransferase, elevated bilirubin, mucositis, cytomegalovirus infection, hemorrhage, diarrhea, hematuria and rash. (6.1)

To report SUSPECTED ADVERSE REACTIONS, contact Shorla Oncology at 844-9-SHORLA or FDA at 1-800-FDA-1088 or www.fda.gov/medwatch.

8 USE IN SPECIFIC POPULATIONS

- Lactation: Advise not to breastfeed. (8.2)
- Moderate or severe renal impairment: Monitor patients more frequently for toxicity. (8.6, 12.3)
- Moderate or severe hepatic impairment: Monitor patients more frequently for toxicity. (8.7, 12.3)

FULL PRESCRIBING INFORMATION

WARNING: SEVERE MYELOSUPPRESSION and CARCINOGENICITY

- TEPYLUTE may cause severe marrow suppression, and high doses may cause marrow ablation with resulting infection or bleeding. Monitor hematologic laboratory parameters. [see Warnings and Precautions (5.1)].
- TEPYLUTE should be considered potentially carcinogenic in humans [see Warnings and Precautions (5.7)].

1 INDICATIONS AND USAGE

1.1 Adenocarcinoma of the Breast or Ovary

TEPYLUTE is indicated for treatment of adenocarcinoma of the breast or ovary.

2 DOSAGE AND ADMINISTRATION

2.1 Recommended Dosage

Adenocarcinoma of the Breast or Ovary

The recommended dose of TEPYLUTE for treatment of adenocarcinoma of the breast or ovary is 0.3 mg/kg to 0.4 mg/kg intravenously. Doses should be given at 1 to 4 week intervals. Initially the higher dose in the given range is commonly administered. The maintenance dose should be adjusted weekly on the basis of pretreatment control blood counts and subsequent blood counts.

Maintenance doses should not be administered more frequently than weekly.

2.2 Preparation Instructions

TEPYLUTE is a hazardous drug. Follow applicable special handling and disposal procedures^1.

Use aseptic technique to prepare TEPYLUTE.

Dilution in the infusion bag

- Remove vial from refrigerated conditions 1 hour prior to dilution.
- Dilute the solution in an appropriate volume of 0.9% Sodium Chloride Injection to obtain a final TEPYLUTE concentration between 0.5 mg/mL and 1 mg/mL. Use a 16G needle with a Luer-lock syringe to dilute the solution.
- Use the diluted TEPYLUTE infusion solution immediately. If the solution is not used immediately, store refrigerated at 2°C to 8°C (36°F to 46°F) for up to 24 hours, or at room temperature 25°C (77°F) for up to 4 hours.

Parenteral drug products should be inspected visually for particulate matter and discoloration prior to administration, whenever solution and container permit. Use TEPYLUTE diluted solutions only if free of visible particulate matter. Filter using a 0.2 micron filter prior to administration. Filtering does not alter solution potency.

Storage of Undiluted TEPYLUTE:

- Single-dose vial: Each vial is intended for single-dose only. Discard any unused portion left in the vial.
- Multiple-dose vial: After first use, store the partially used vial in the original carton refrigerated at 2°C to 8°C (36°F to 46°F) for up to 28 days.

3 DOSAGE FORMS AND STRENGTHS

- Injection: 15 mg/1.5 mL (10 mg/mL) of thiotepa in a clear, colorless or almost colorless solution in single-dose vial.
- Injection: 100 mg/10 mL (10 mg/mL) of thiotepa in a clear, colorless or almost colorless solution in multiple-dose vial.

4 CONTRAINDICATIONS

TEPYLUTE is contraindicated in:

- Patients with severe hypersensitivity to thiotepa [see Warnings and Precautions (5.2)]
- Concomitant use with live or attenuated vaccines [see Warnings and Precautions (5.4)]

5 WARNINGS AND PRECAUTIONS

5.1 Myelosuppression

For patients receiving TEPYLUTE for treatment of adenocarcinoma of the breast or adenocarcinoma of the ovary, if the bone marrow has been compromised by prior irradiation or chemotherapy, or is recovering from chemotherapy, the risk of severe myelosuppression with TEPYLUTE may be increased. Perform periodic complete blood counts during the course of treatment with TEPYLUTE. Provide supportive care for infections, bleeding, and symptomatic anemia [see Adverse Reactions (6.1)].

5.2 Hypersensitivity

Clinically significant hypersensitivity reactions, including anaphylaxis, have occurred following administration of thiotepa. If anaphylactic or other clinically significant allergic reaction occurs, discontinue treatment with TEPYLUTE, initiate appropriate therapy, and monitor until signs and symptoms resolve [see Contraindications (4) and Adverse Reactions (6.1)].

5.3 Cutaneous Toxicity

TEPYLUTE and/or its active metabolites may be excreted in part via skin in patients receiving high-dose therapy. Treatment with TEPYLUTE may cause skin discoloration, pruritus, blistering, desquamation, and peeling that may be more severe in the groin, axillae, skin folds, in the neck area, and under dressings. Instruct patients to shower or bathe with water at least twice daily through 48 hours after administration of TEPYLUTE. Change occlusive dressing and clean the covered skin at least twice daily through 48 hours after administration of TEPYLUTE. Change bed sheets daily during treatment.

Skin reactions associated with accidental exposure to TEPYLUTE may occur. Wash the skin thoroughly with soap and water in case TEPYLUTE solution contacts the skin. Flush mucous membranes in case of TEPYLUTE contact with mucous membranes.

5.4 Concomitant Use of Live and Attenuated Vaccines

Do not administer live or attenuated viral or bacterial vaccines to a patient treated with TEPYLUTE until the immunosuppressive effects have resolved.

5.5 Hepatic Veno-Occlusive Disease

Monitor by physical examination, serum transaminases and bilirubin, and provide supportive care to patients who develop hepatic veno-occlusive disease.

5.6 Central Nervous System Toxicity

Fatal encephalopathy has occurred in patients treated with high doses of thiotepa. Other central nervous system toxicities, such as headache, apathy, psychomotor retardation, disorientation, confusion, amnesia, hallucinations, drowsiness, somnolence, seizures, coma, inappropriate behavior and forgetfulness have been reported to occur in a dose-dependent manner during or shortly after administration of high-dose thiotepa. Do not exceed the recommended dose of TEPYLUTE. If severe or life-threatening central nervous system toxicity occurs, discontinue administration of TEPYLUTE and provide supportive care.

5.7 Carcinogenicity

Like many alkylating agents, thiotepa has been reported to be carcinogenic when administered to laboratory animals [see Nonclinical Toxicity (13.1)]. Carcinogenicity is shown most clearly in studies using mice, but there is some evidence of carcinogenicity in man. There is an increased risk of a secondary malignancy with use of TEPYLUTE.

5.8 Polyethylene Glycol 400 Toxicity

TEPYLUTE contains a high concentration of polyethylene glycol (PEG) 400. Based on findings in animals, administration of high amounts of PEG 400 may cause damage to the kidneys and liver at dosages higher than recommended. When prescribing TEPYLUTE, take into consideration the PEG 400 load from concomitant medications.

5.9 Embryo-Fetal Toxicity

Based on the mechanism of action and findings in animals, TEPYLUTE can cause fetal harm when administered to a pregnant woman. There are no adequate and well-controlled studies of TEPYLUTE in pregnant women. Thiotepa given by the intraperitoneal (IP) route was teratogenic in mice at doses ≥ 1 mg/kg (3.2 mg/m^2), approximately 8-fold less than the maximum recommended human therapeutic dose (0.8 mg/kg, 27 mg/m^2), based on body-surface area. Thiotepa given by the IP route was teratogenic in rats at doses ≥ 3 mg/kg (21 mg/m^2), approximately equal to the maximum recommended human therapeutic dose, based on body-surface area. Thiotepa was lethal to rabbit fetuses at a dose of 3 mg/kg (41 mg/m^2), approximately two times the maximum recommended human therapeutic dose based on body-surface area.

Advise pregnant women of the potential risk to the fetus [see Use in Specific Populations (8.1, 8.3)]. Advise females of reproductive potential to use highly effective contraception during and after treatment with TEPYLUTE for 6 months after therapy. Advise males of reproductive potential to use effective contraception during and after treatment with TEPYLUTE for 1 year after therapy [see Use in Specific Populations (8.1, 8.3)].

6 ADVERSE REACTIONS

The following clinically significant adverse reactions are described elsewhere in other sections of the label:

- Myelosuppression [see Warnings and Precautions (5.1)]
- Infection [see Warnings and Precautions (5.1)]
- Hypersensitivity [see Warnings and Precautions (5.2)]
- Cutaneous Toxicity [see Warnings and Precautions (5.3)]
- Hepatic Veno-Occlusive Disease [see Warnings and Precautions (5.5)]
- Central Nervous System Toxicity [see Warnings and Precautions (5.6)]
- Carcinogenicity [see Warnings and Precautions (5.7)]

6.1 Clinical Trials Experience

Because clinical trials are conducted under widely varying conditions, adverse reaction rates observed in the clinical trials of a drug cannot be directly compared with rates in the clinical trials of another drug and may not reflect the rates observed in practice.

Adverse Reactions with Treatment of adenocarcinoma of the breast and adenocarcinoma of the ovary

Gastrointestinal: Nausea, vomiting, abdominal pain, anorexia.

General: Fatigue, weakness. Febrile reaction and discharge from a subcutaneous lesion may occur as the result of breakdown of tumor tissue.

Hypersensitivity Reactions: Allergic reactions - rash, urticaria, laryngeal edema, asthma, anaphylactic shock, wheezing.

Local Reactions: Contact dermatitis, pain at the injection site.

Neurologic: Dizziness, headache, blurred vision.

Renal: Dysuria, urinary retention, chemical cystitis or hemorrhagic cystitis.

Reproductive: Amenorrhea, interference with spermatogenesis.

Respiratory: Prolonged apnea has been reported when succinylcholine was administered prior to surgery, following combined use of thiotepa and other anticancer agents. It was theorized that this was caused by decrease of pseudocholinesterase activity caused by the anticancer drugs.

Skin: Dermatitis, alopecia. Skin depigmentation has been reported following topical use.

Special Senses: Conjunctivitis.

6.2 Postmarketing Experience

The following adverse reactions have been identified during post approval use of thiotepa. Because these reactions are reported voluntarily from a population of uncertain size, it is not always possible to reliably estimate their frequency or establish a causal relationship to drug exposure.

Blood and lymphatic system disorders: Febrile bone marrow aplasia.

Cardiac disorders: Bradycardia, cardiac failure congestive, cardio-respiratory arrest, pericardial effusion, pericarditis, right ventricular hypertrophy.

Congenital, familial and genetic disorders: Aplasia.

Ear and labyrinth disorders: Deafness.

Eye disorders: Blindness, eyelid ptosis, papilledema, strabismus.

Gastrointestinal disorders: Ascites, dysphagia, enterocolitis, gastritis, palatal disorder.

General disorders and administration site conditions: Device related infection, gait disturbance, malaise, multi-organ failure, pain.

Hepatobiliary disorders: Hepatomegaly.

Immune system disorders: Bone marrow transplant rejection, immunosuppression.

Infections and infestations: Acute sinusitis, bronchopulmonary aspergillosis, candida sepsis, enterococcal infection, Epstein-Barr virus infection, Escherichia sepsis, Fusarium infection, gastroenteritis, infection, lower respiratory tract infection fungal, lower respiratory tract infection viral, parainfluenza virus infection, Pneumonia legionella, relapsing fever, respiratory tract infection, sepsis, septic shock, Staphylococcal bacteremia, Staphylococcal infection, systemic candida, urinary tract infection.

Injury, poisoning and procedural complications: Refractoriness to platelet transfusion, subdural hematoma.

Investigations: Coagulation test abnormal, hemoglobin decreased, Klebsiella test positive, nuclear magnetic resonance imaging brain abnormal, transaminases increased, weight increased.

Metabolism and nutrition disorders: Hyponatremia.

Neoplasms benign, malignant and unspecified (incl. cysts and polyps): Breast cancer metastatic, central nervous system lymphoma, leukemia recurrent, lymphoma, malignant neoplasm progression, metastatic neoplasm, post-transplant lymphoproliferative disorder.

Nervous system disorders: Aphasia, brain injury, bulbar palsy, central nervous system lesion, cerebral microangiopathy, cerebral ventricle dilatation, cerebrovascular accident, cognitive disorder, convulsion, coordination abnormal, encephalitis, encephalopathy, hemiplegia, hypotonia, leukoencephalopathy, memory impairment, motor dysfunction, neurotoxicity, quadriparesis, speech disorder, tremor, VIIth nerve paralysis, white matter lesion.

Psychiatric disorders: Delirium, depression, disorientation, suicidal ideation.

Renal and urinary disorders: Renal failure, nephropathy toxic.

Respiratory, thoracic and mediastinal disorders: Acute respiratory distress, aspiration, dyspnea exertional, interstitial lung disease, lung disorder, pneumonitis, pulmonary arteriopathy, pulmonary sepsis, pulmonary veno-occlusive disease, respiratory distress, respiratory failure, pulmonary hypertension.

Skin and subcutaneous tissue disorders: Stevens-Johnson syndrome and toxic epidermal necrolysis.

Vascular disorders: Capillary leak syndrome.

7 DRUG INTERACTIONS

7.1 Effect of Cytochrome CYP3A Inhibitors and Inducers

In vitro studies suggest that thiotepa is metabolized by CYP3A4 and CYP2B6 to its active metabolite TEPA. Avoid coadministration of strong CYP3A4 inhibitors (e.g., itraconazole, clarithromycin, ritonavir) and strong CYP3A4 inducers (e.g., rifampin, phenytoin) with thiotepa due to the potential effects on efficacy and toxicity [see Clinical Pharmacology (12.3)]. Consider alternative medications with no or minimal potential to inhibit or induce CYP3A4. If concomitant use of strong CYP3A4 modulators cannot be avoided, closely monitor for adverse drug reactions.

7.2 Effect of TEPYLUTE on Cytochrome CYP2B6 Substrates

In vitro studies suggest that thiotepa inhibits CYP2B6. Thiotepa may increase the exposure of drugs that are substrates of CYP2B6 in patients; however, the clinical relevance of this in vitro interaction is unknown [see Clinical Pharmacology (12.3)]. The administration of thiotepa with cyclophosphamide in patients reduces the conversion of cyclophosphamide to the active metabolite, 4-hydroxycyclophosphamide; the effect appears sequence dependent with a greater reduction in the conversion to 4-hydroxycyclophosphamide when thiotepa is administered 1.5 hours prior to the intravenous administration of cyclophosphamide compared to administration of thiotepa after intravenous cyclophosphamide [see Clinical Pharmacology (12.3)]. The reduction in 4-hydroxycyclophosphamide levels may potentially reduce efficacy of cyclophosphamide treatment.

8 USE IN SPECIFIC POPULATIONS

8.1 Pregnancy

Risk Summary

TEPYLUTE can cause fetal harm when administered to a pregnant woman based on findings from animals and the drug’s mechanism of action [see Clinical Pharmacology (12.1)]. Limited available data with thiotepa use in pregnant women are insufficient to inform a drug-associated risk of major birth defects and miscarriage. In animal reproduction studies, administration of thiotepa to pregnant mice and rats during organogenesis produced teratogenic effects (neural tube defects and malformations of the skeletal system of the fetus) at doses approximately 0.125 and 1 times, respectively, the maximum recommended human daily dose on a mg/m^2 basis. Thiotepa was lethal to rabbit fetuses at approximately 2 times the maximum recommended human therapeutic dose based on body-surface area [see Data]. Consider the benefits and risks of TEPYLUTE for the mother and possible risks to the fetus when prescribing TEPYLUTE to a pregnant woman.

The estimated background risk of major birth defects and miscarriage for the indicated population is unknown. In the U.S. general population, the estimated background risk of major birth defects and miscarriage in clinically recognized pregnancies is 2-4% and 15-20%, respectively.

Data

Animal Data

Thiotepa given by the IP route in mice at doses ≥ 1 mg/kg (3.2 mg/m^2), approximately 8-fold less than the maximum recommended human therapeutic dose based on body-surface area, and in rats at doses ≥ 3 mg/kg (21 mg/m^2), approximately equal to the maximum recommended human therapeutic dose based on body-surface area, resulted in various malformations including neural tube defects, omphalocele, renal agenesis, atresia ani, limb and digit defects, cleft palate, micrognathia, other skeletal anomalies in the skull, vertebrae and ribs, and reduced skeletal ossification. Thiotepa was lethal to rabbit fetuses at a dose of 3 mg/kg (41 mg/m^2), approximately 2 times the maximum recommended human therapeutic dose based on body-surface area.

8.2 Lactation

Risk Summary

There is no information regarding the presence of thiotepa in human milk, the effects on the breastfed infant, or the effects on milk production.

Because of the potential for serious adverse reactions, including the potential for tumorigenicity shown for thiotepa in animal studies, advise patients not to breastfeed during TEPYLUTE treatment and for 1 week after the last dose.

8.3 Females and Males of Reproductive Potential

TEPYLUTE can cause fetal harm when administered to a pregnant woman [see Use in Specific Populations (8.1)].

Pregnancy testing

Verify the pregnancy status of females of reproductive potential prior to initiating TEPYLUTE therapy.

Contraception

Females

Advise females of reproductive potential to avoid pregnancy during TEPYLUTE treatment and for 6 months after the last dose of TEPYLUTE. Advise females to immediately report pregnancy [see Use in Specific Populations (8.1)].

Males

TEPYLUTE may damage spermatozoa and testicular tissue, resulting in possible genetic abnormalities. Males with female sexual partners of reproductive potential should use effective contraception during TEPYLUTE treatment and for 1 year after the last dose of TEPYLUTE [see Nonclinical Toxicology (13.1)].

Infertility

Based on nonclinical findings, male and female fertility may be compromised by treatment with TEPYLUTE. Inform male patients about the possibility of sperm conservation before the start of therapy [see Nonclinical Toxicology (13.1)].

8.4 Pediatric Use

Safety and effectiveness of TEPYLUTE in neonates have not been established.

Safety and effectiveness of TEPYLUTE for treatment of adenocarcinoma of the breast and adenocarcinoma of the ovary in pediatric patients have not been established.

8.5 Geriatric Use

Clinical studies of thiotepa for treatment of adenocarcinoma of the breast and adenocarcinoma of the ovary did not include sufficient numbers of subjects aged 65 and over to determine whether elderly subjects respond differently from younger subjects, and other reported clinical experience has not identified differences in responses between the elderly and younger patients. In general, dose selection for an elderly patient should be cautious, usually starting at the low end of the dosing range, reflecting the greater frequency of decreasing hepatic, renal or cardiac function, and of concomitant disease or other drug therapy.

8.6 Renal Impairment

In patients with moderate (creatinine clearance (CLcr) of 30 mL/min to 59 mL/min) renal impairment, decreased renal excretion may result in increased plasma levels of thiotepa and TEPA [see Clinical Pharmacology (12.3)]. This may result in increased toxicity. Monitor patients with moderate to severe (CLcr < 30 mL/min) renal impairment for signs and symptoms of toxicity following treatment with TEPYLUTE for an extended period of time.

8.7 Hepatic Impairment

Thiotepa is extensively metabolized in the liver. Patients with moderate (bilirubin levels greater than 1.5 times to 3 times the upper limit of normal and any AST) hepatic impairment may have increased plasma levels of thiotepa [see Clinical Pharmacology (12.3)]. This may result in toxicity. Monitor patients with moderate to severe (bilirubin levels greater than 3 times upper limit of normal and any AST) hepatic impairment for signs and symptoms of toxicity following treatment with TEPYLUTE for an extended period of time.

10 OVERDOSAGE

There is no experience with overdoses of thiotepa. The most important adverse reactions expected in case of overdose are myeloablation and pancytopenia [see Nonclinical Toxicology (13.1)]. There is no known antidote for thiotepa. Monitor the hematological status closely and provide vigorous supportive measures as medically indicated.

11 DESCRIPTION

TEPYLUTE injection contains thiotepa, an alkylating drug. The chemical name for thiotepa is Tris(1-aziridinyl)phosphine sulfide. Thiotepa has the following structural formula:

Thiotepa has the molecular formula C6 H12 N3 PS, and a molecular weight of 189.23, and it appears as fine, white crystalline flakes, with a melting range of 52°C to 57°C. It is soluble in water and organic solvents. Thiotepa is unstable in acid medium.

TEPYLUTE (thiotepa) injection is supplied as a sterile solution for intravenous use after dilution. When diluted in water, the resulting solution has a pH of approximately 5.5 to 7.5.

TEPYLUTE injection is a 10 mg/mL solution available as:

- 15 mg/1.5 mL strength single-dose vial contains 15 mg thiotepa and 1.7 g of polyethylene glycol 400
- 100 mg/10 mL strength multiple-dose vial contains 100 mg thiotepa and 11.3 g of polyethylene glycol 400

12 CLINICAL PHARMACOLOGY

12.1 Mechanism of Action

Thiotepa is an alkylating drug of the polyfunctional type, related chemically and pharmacologically to the nitrogen mustard. The radiomimetic action of thiotepa is believed to occur through the release of ethyleneimine radicals which, like irradiation, disrupt the bonds of DNA. One of the principle bond disruptions is initiated by alkylation of guanine at the N-7 position, which severs the linkage between the purine base and the sugar and liberates alkylated guanines.

12.3 Pharmacokinetics

Absorption

Thiotepa reached maximal concentrations close to the end of infusion following an intravenous infusion.

Distribution

The binding of thiotepa to plasma proteins is approximately 10% to 20%. In adults administered intravenous thiotepa between 20 mg to 250 mg/m^2 as an intravenous bolus or infusion up to 4 hours, the mean volume of distribution of thiotepa ranged from 1.0 L/kg (30%) to 1.9 L/kg (17%).

Elimination

In adults administered intravenous thiotepa between 20 mg to 250 mg/m^2 as an intravenous bolus or infusion up to 4 hours, the mean thiotepa clearance ranged from 14.6 L/hr/m^2 (23%) to 27.9 L/hr/m^2 (69%). In adult population, the mean terminal elimination half-life ranged from 1.4 hours (7%) to 3.7 hours (14%) for thiotepa and from 4.9 hours to 17.6 hours (20%) for TEPA.

Metabolism

Thiotepa undergoes hepatic metabolism. In vitro data suggests that CYP3A4 and CYP2B6 may be responsible for the metabolism of thiotepa to TEPA, a major active metabolite.

Excretion

In adult patients, urinary excretion of thiotepa accounted for less than 2% of the dose and TEPA accounted for 11% or less of the dose.

Specific Populations

Hepatic Impairment

The exposure (as measured by area under the curve (AUC)) of thiotepa increased by 1.6-fold and 1.8-fold following administration of multiple thiotepa doses of 7 mg/kg administered every 2 days with cyclophosphamide in two adult patients who had liver metastases with moderate hepatic impairment compared to the exposure observed in one patient with normal hepatic function. The effect of severe hepatic impairment on thiotepa exposure is unknown.

Renal Impairment

The exposure (as measured by AUC) of thiotepa increased by 1.4-fold and TEPA increased by 2.6-fold following administration of multiple doses of 120 mg/m^2/day in one patient with moderate renal impairment (CLcr = 38 mL/min) administered cyclophosphamide plus thiotepa plus carboplatin, compared to exposure of thiotepa in patients with normal renal function. The effects of severe renal impairment or end-stage renal disease on thiotepa exposure are unknown.

Drug Interactions

The clinical relevance of in vitro inhibition of the cytochrome P450 enzymes described below is unknown, but it cannot be excluded that the systemic exposure of thiotepa or medicinal products that are substrates for these enzymes may be affected with concomitant administration with TEPYLUTE.

Effect of Cytochrome P450 Modulators on Thiotepa

In vitro data demonstrates that CYP3A4 and CYP2B6 inhibitors decrease the metabolism of thiotepa [see Drug Interactions (7.1)].

Effect of Thiotepa on Cytochrome P450 2B6

In vitro data demonstrates that thiotepa inhibits CYP2B6.

Effect of Thiotepa on Cyclophosphamide

The administration of thiotepa 1.5 hours prior to intravenous cyclophosphamide in patients administered cyclophosphamide plus thiotepa plus carboplatin decreased the AUC of 4-hydroxycyclophosphamide by 26% and maximal concentrations of 4-hydroxycyclophosphamide by 62%, compared to administration of cyclophosphamide prior to thiotepa.

13 NONCLINICAL TOXICOLOGY

13.1 Carcinogenesis, Mutagenesis, Impairment of Fertility

In mice, repeated intraperitoneal (IP) administration of thiotepa (1.15 or 2.3 mg/kg three times per week for 52 or 43 weeks, respectively) produced a significant increase in the combined incidence of squamous-cell carcinomas of the skin, preputial gland, and ear canal, and combined incidence of lymphoma and lymphocytic leukemia. In other studies in mice, repeated IP administration of thiotepa (4 or 8 mg/kg three times per week for 4 weeks followed by a 20 week observation period or 1.8 mg/kg three times per week for 4 weeks followed by a 35 week observation period) resulted in an increased incidence of lung tumors. In rats, repeated IP administration of thiotepa (0.7 or 1.4 mg/kg three times per week for 52 or 34 weeks, respectively) produced significant increases in the incidence of squamous-cell carcinomas of the skin or ear canal, combined hematopoietic neoplasms, and uterine adenocarcinomas. Thiotepa given intravenously (IV) to rats (1 mg/kg once per week for 52 weeks) produced an increased incidence of malignant tumors (abdominal cavity sarcoma, lymphosarcoma myelosis, seminoma, fibrosarcoma, salivary gland hemangioendothelioma, mammary sarcoma, pheochromocytoma) and benign tumors. The lowest reported carcinogenic dose in mice (1.15 mg/kg, 3.68 mg/m^2) is approximately 7-fold less than the maximum recommended human therapeutic dose based on body-surface area. The lowest reported carcinogenic dose in rats (0.7 mg/kg, 4.9 mg/m ^2) is approximately 6-fold less than the maximum recommended human therapeutic dose based on body-surface area.

Thiotepa was mutagenic in in vitro assays in Salmonella typhimurium, E coli, Chinese hamster lung and human lymphocytes. Chromosomal aberrations and sister chromatid exchanges were observed in vitro with thiotepa in bean root tips, human lymphocytes, Chinese hamster lung, and monkey lymphocytes.

Mutations were observed with oral thiotepa in mouse at doses > 2.5 mg/kg (8 mg/m^2). The mouse micronucleus test was positive with intraperitoneal administration of > 1 mg/kg (3.2 mg/m^2). Other positive in vivo chromosomal aberration or mutation assays included Drosophila melanogaster, Chinese hamster marrow, murine marrow, monkey lymphocyte, and murine germ cell.

Thiotepa impaired fertility in male mice at oral or intraperitoneal doses ≥ 0.7 mg/kg (2.24 mg/m^2), approximately 12-fold less than the maximum recommended human therapeutic dose based on body-surface area. Thiotepa (0.5 mg) inhibited implantation in female rats when instilled into the uterine cavity. Thiotepa interfered with spermatogenesis in mice at IP doses ≥ 0.5 mg/kg (1.6 mg/m^2), approximately 17-fold less than the maximum recommended human therapeutic dose based on body-surface area. Thiotepa interfered with spermatogenesis in hamsters at an IP dose of 1 mg/kg (4.1 mg/m^2), approximately 7-fold less than the maximum recommended human therapeutic dose based on body-surface area.

15 REFERENCES

1. OSHA Hazardous Drugs. OSHA. [Accessed from http://www.osha.gov/SLTC/hazardousdrugs/index.html].

16 HOW SUPPLIED/STORAGE AND HANDLING

How Supplied

TEPYLUTE injection is supplied as a clear, colorless or almost colorless solution. The vial stopper is not made with natural rubber latex.

TEPYLUTE Injection

NDC Number | Strength | Vial Presentation
81927-105-01 | 15 mg/ 1.5 mL (10 mg/mL) | Single-dose vial, carton of 1
81927-106-01 | 100 mg/ 10 mL (10 mg/mL) | Multiple-dose vial, carton of 1

Storage and Handling

TEPYLUTE injection vials must be stored and transported refrigerated at 2°C to 8°C (36°F to 46°F). Do not freeze.

TEPYLUTE injection is a hazardous drug. Follow applicable special handling and disposal procedures^1.

17 PATIENT COUNSELING INFORMATION

Hypersensitivity

Counsel patients on the signs and symptoms of hypersensitivity and to seek immediate emergency assistance if they develop any of these signs and symptoms [see Warnings and Precautions (5.2)].

Myelosuppression

Inform patients of the possibility of developing low blood cell counts and the need for hematopoietic progenitor cell infusion. Instruct patients to immediately report to their healthcare provider if bleeding or fever occurs [see Warnings and Precautions (5.1)].

Embryo-Fetal Toxicity

Advise pregnant women and females of reproductive potential of the potential risk to a fetus. Advise females of reproductive potential to inform their healthcare provider if they are pregnant or become pregnant.

Advise females of reproductive potential to use effective contraception during treatment with TEPYLUTE and for 6 months after the last dose [see Warnings and Precautions (5.7), Use in Specific Populations (8.1, 8.3)].

Advise males with female partners of reproductive potential to use effective contraception during TEPYLUTE treatment and for 1 year after the last dose of TEPYLUTE [see Use in Specific Populations (8.3)].

Advise patients that TEPYLUTE can produce infertility. Inform male patients about the possibility of sperm conservation before the start of therapy [see Use in Specific Populations (8.3)].

Lactation

Advise women not to breastfeed while receiving TEPYLUTE and for 1 week after the last dose [see Use in Specific Populations (8.2)].

Secondary malignancies

Inform patients that TEPYLUTE can increase the risk of secondary malignancy [see Warnings and Precautions (5.5)].

Manufactured by:

AqVida GmbH, Dassow,

Germany

Distributed by:

Shorla Oncology Inc.,

Cambridge, MA 02142, USA

Patent Information: U.S. Patent: 11,975,013

Version: THTGIUS008

Principal Display Panel - 15 mg/1.5 mL Vial Label

NDC 81927-105-01

Rx Only

Tepylute®

(thiotepa) injection

15 mg/1.5 mL

(10 mg/mL)

For intravenous infusion.
MUST BE DILUTED PRIOR TO USE.

Single-dose vial

Discard unused portion

Principal Display Panel - 15 mg/1.5 mL Carton

NDC 81927-105-01

Rx Only

Tepylute®

(thiotepa) injection

15 mg/1.5 mL

(10 mg/mL)

For Intravenous Infusion.

MUST BE DILUTED PRIOR TO USE.

WARNING: Hazardous Drug

Contains one single-dose vial

Discard unused portion

Sterile

Principal Display Panel - 100 mg/10 mL Vial Label

NDC 81927-106-01

Rx Only

Tepylute®

(thiotepa) injection

100 mg/10 mL

(10 mg/mL)

For intravenous infusion.
MUST BE DILUTED PRIOR TO USE.

Multiple-Dose vial

Principal Display Panel - 100 mg/10 mL Carton

NDC 81927-106-01

Rx Only

Tepylute®

(thiotepa) injection

100 mg/10 mL

(10 mg/mL)

For Intravenous Infusion.

MUST BE DILUTED PRIOR TO USE.

WARNING: Hazardous Drug

Contains one Multiple-Dose vial

Sterile